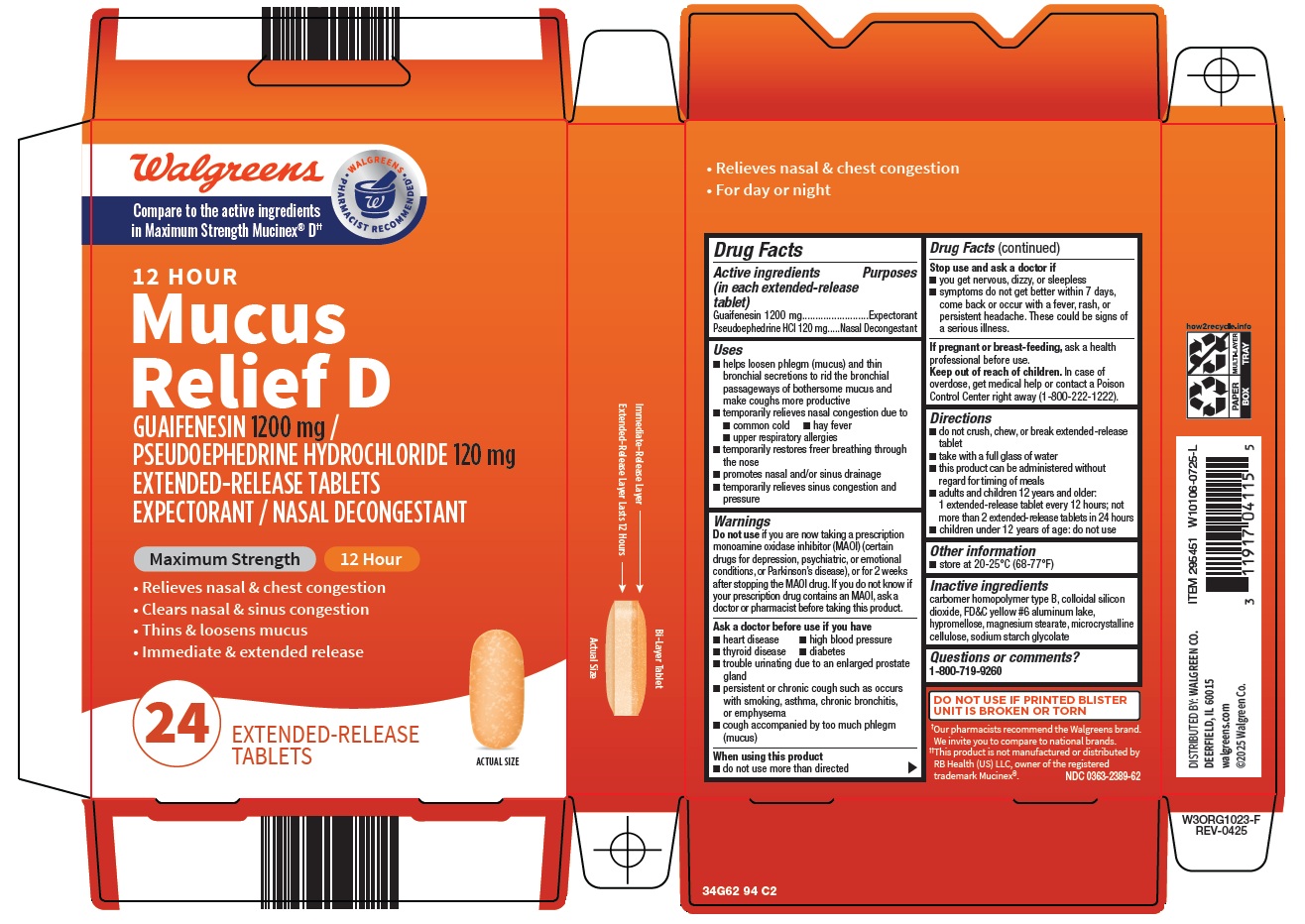 DRUG LABEL: mucus relief d
NDC: 0363-2389 | Form: TABLET, MULTILAYER, EXTENDED RELEASE
Manufacturer: Walgreen Company
Category: otc | Type: HUMAN OTC DRUG LABEL
Date: 20260207

ACTIVE INGREDIENTS: GUAIFENESIN 1200 mg/1 1; PSEUDOEPHEDRINE HYDROCHLORIDE 120 mg/1 1
INACTIVE INGREDIENTS: CARBOMER HOMOPOLYMER TYPE B (ALLYL PENTAERYTHRITOL CROSSLINKED); SILICON DIOXIDE; FD&C YELLOW NO. 6 ALUMINUM LAKE; HYPROMELLOSE, UNSPECIFIED; MAGNESIUM STEARATE; MICROCRYSTALLINE CELLULOSE; SODIUM STARCH GLYCOLATE TYPE A

Walgreen Co. Mucus Relief D Drug Facts

Active ingredients (in each extended-release tablet)

Guaifenesin 1200 mg

Pseudoephedrine HCl 120 mg

Purposes

Expectorant

Nasal Decongestant

Uses

- helps loosen phlegm (mucus) and thin bronchial secretions to rid the bronchial passageways of bothersome mucus and make coughs more productive
- temporarily relieves nasal congestion due to
  - common cold
  - hay fever
  - upper respiratory allergies
- temporarily restores freer breathing through the nose
- promotes nasal and/or sinus drainage
- temporarily relieves sinus congestion and pressure

Warnings

Do not use

if you are now taking a prescription monoamine oxidase inhibitor (MAOI) (certain drugs for depression, psychiatric or emotional conditions, or Parkinson’s disease), or for 2 weeks after stopping the MAOI drug. If you do not know if your prescription drug contains an MAOI, ask a doctor or pharmacist before taking this product.

Ask a doctor before use if you have

- heart disease
- high blood pressure
- thyroid disease
- diabetes
- trouble urinating due to an enlarged prostate gland
- persistent or chronic cough such as occurs with smoking, asthma, chronic bronchitis, or emphysema
- cough accompanied by too much phlegm (mucus)

When using this product

- do not use more than directed

Stop use and ask a doctor if

- you get nervous, dizzy, or sleepless
- symptoms do not get better within 7 days, come back or occur with a fever, rash, or persistent headache. These could be signs of a serious illness.

If pregnant or breast-feeding,

ask a health professional before use.

Keep out of reach of children.

In case of overdose, get medical help or contact a Poison Control Center right away (1-800-222-1222).

Directions

- do not crush, chew, or break extended-release tablet
- take with a full glass of water
- this product can be administered without regard for timing of meals
- adults and children 12 years and older:
1 extended-release tablet every 12 hours; not more than 2 extended-release tablets in 24 hours
- children under 12 years of age: do not use

Other information

- store at 20-25°C (68-77°F)

Inactive ingredients

carbomer homopolymer type B, colloidal silicon dioxide, FD&C yellow #6 aluminum lake, hypromellose, magnesium stearate, microcrystalline cellulose, sodium starch glycolate

Package/Label Principal Display Panel

Walgreens

WALGREENS • PHARMACIST RECOMMENDED •

Compare to the active ingredients in Maximum Strength Mucinex® D

12 HOUR

Mucus Relief D

GUAIFENESIN 1200 mg / PSEUDOEPHEDRINE HYDROCHLORIDE 120 mg

EXTENDED-RELEASE TABLETS

EXPECTORANT / NASAL DECONGESTANT

Maximum Strength

12 Hour

• Relieves nasal & chest congestion

• Clears nasal & sinus congestion

• Thins & loosens mucus

• Immediate & extended release

24 EXTENDED-RELEASE TABLETS

ACTUAL SIZE